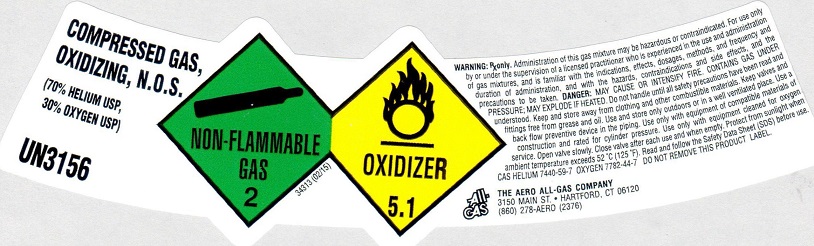 DRUG LABEL: Oxygen Helium Mixture 30/70
NDC: 10014-018 | Form: GAS
Manufacturer: Aero All Gas Company
Category: prescription | Type: HUMAN PRESCRIPTION DRUG LABEL
Date: 20171218

ACTIVE INGREDIENTS: OXYGEN 300 mL/1 L
INACTIVE INGREDIENTS: HELIUM 700 mL/1 L

O2 30 HE 70 MIX

PACKAGE LABEL

COMPRESSED GAS, N.O.S. (70% HELIUM USP, 30% OXYGEN USP) UN3156 NON-FLAMMABLE GAS 2 OXIDIZER 5.1
Rx only WARNING: Administration of this gas mixture may be hazardous or contraindicated. For use only by or under the supervision of a licensed practitioner who is experienced in the use and administration of gas mixtures and is familiar with the indications, effects, dosages, methods, and frequency and duration of administration, and with the hazards, contraindications, and side effects and the precautions to be taken.
DANGER: MAY CAUSE OR INTENSIFY FIRE. CONTAINS GAS UNDER PRESSURE; MAY EXPLODE IF HEATED. Do not handle until all safety precautions have been read and understood. Keep and store away from clothing and other combustible materials. Keep valves and fittings free from grease and oil. Use and store only outdoors or in a well ventilated place. Use a back flow preventive device in the piping. Use only with equipment rated for cylinder pressure. Use only with equipment cleaned for oxygen service. Open valve slowly. Close valve after each use and when empty. Protect from sunlight when ambient temperature exceeds 52 degrees C (125 degrees F). Read and follow the Safety Data Sheet (SDS) before use. CAS HELIUM 7440-59-7 OXYGEN 7782-44-7 DO NOT REMOVE THIS PRODUCT LABEL.
ALL-GAS THE AERO ALL-GAS COMPANY 3150 MAIN ST. . HARTFORD, CT 06120 (860) 278-AERO (2376)